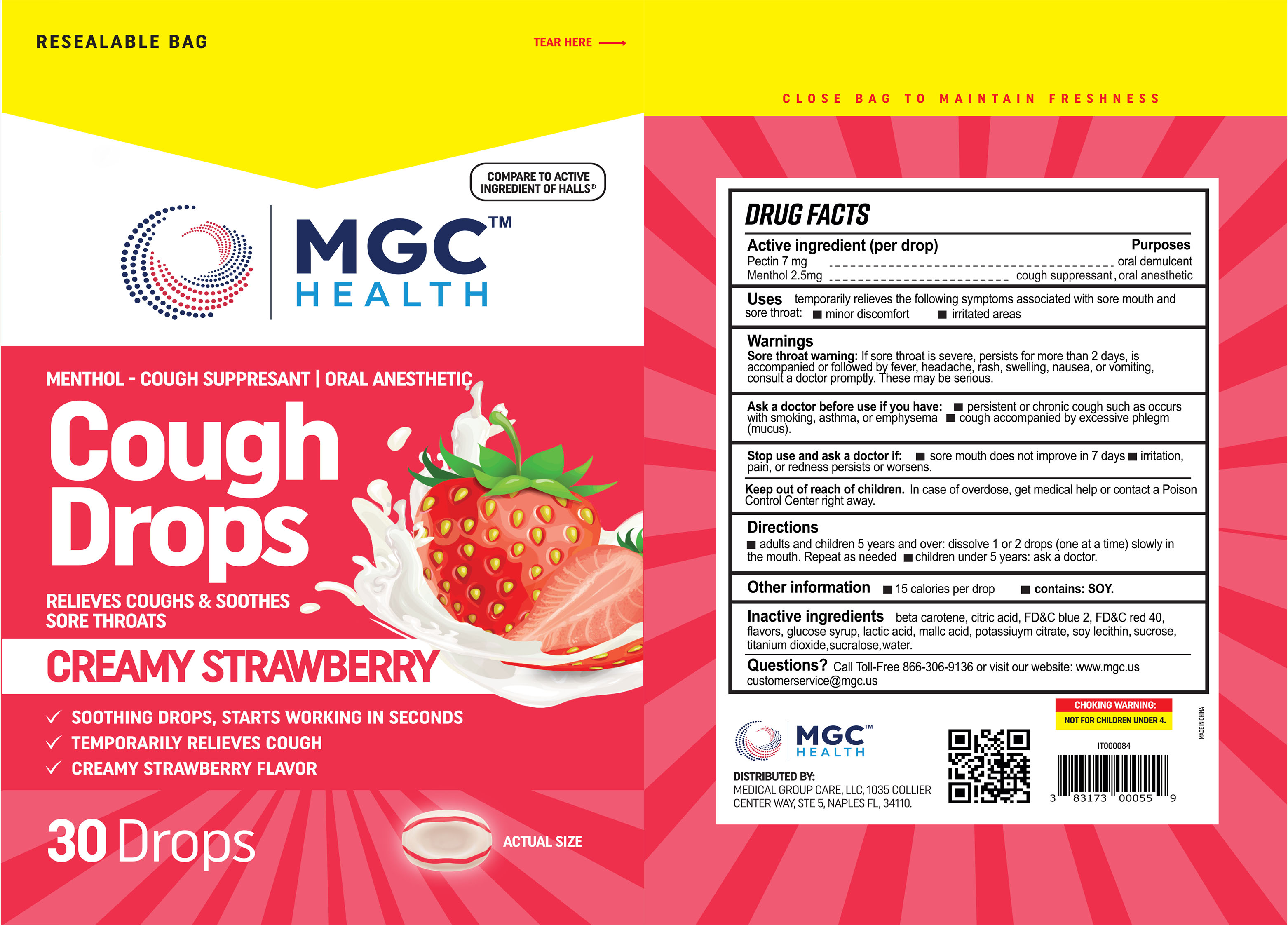 DRUG LABEL: MGC Health
NDC: 83698-129 | Form: LOZENGE
Manufacturer: Xiamen Kang Zhongyuan Biotechnology Co., Ltd.
Category: otc | Type: HUMAN OTC DRUG LABEL
Date: 20251229

ACTIVE INGREDIENTS: MENTHOL 2.5 mg/1 1; PECTIN 7 mg/1 1
INACTIVE INGREDIENTS: SUCROSE; WATER; CITRIC ACID MONOHYDRATE; CORN SYRUP; BETA CAROTENE; LACTIC ACID; POTASSIUM CITRATE; LECITHIN, SOYBEAN; FD&C BLUE NO. 2; FD&C RED NO. 40; SODIUM CHLORIDE; SUCRALOSE; MALIC ACID; TITANIUM DIOXIDE

YNBY-MGC CS Drops 30 2023

Active Ingredient(s)

Menthol 2.5 mg

Pactin 7 mg

Purpose

Pectin: oral demulcent

Menthol: cough suppressant, oral anesthetic

Use

temporarily relieves the following symptoms associated with sore mouth and sore throat:

minor discomfort

irritated areas

Warnings

Sore throat warning: If sore throat is severe, persists for more than 2 days, is accompanied or follow headache, rash, swelling, nausea, or vomiting, consult a doctor promptly. These may be serious.

Ask a doctor before use if you have: ■ persistent or chronic cough such as occurs with smoking, asthma, or emphysema ■ cough accompanied by excessive phlegm (mucus).

Stop use and ask a doctor if ■ sore mouth does not improve in 7 days m, irritation, pain, or redness persists or worsens.

Keep out of reach of children. In case of overdose, get medical help or contact a Poison Control Center right away.

Directions

adults and children 5 ears and over: dissolve 1 or 2 drops (one at a time) slowly in the mouth. Repeat as needed

children under 5 years: ask a doctor.

Other information

■ 15 calories per drop ■ contains: SOY.

Inactive ingredients

beta carotene, citric acid, FD&C blue 2, FD&C red 40, flavors, glucose syrup, lactic acid, malle acid, potassium citrate, soy lecithin, sucrose, titanium dioxide,sucralose, water.

QUESTIONS

Call Toll-Free 866-306-9136 or visit our website: www.mgc.us

customerservice@mgc.us

Package Label - Principal Display Panel

30 Drops NDC: 61658-129-30